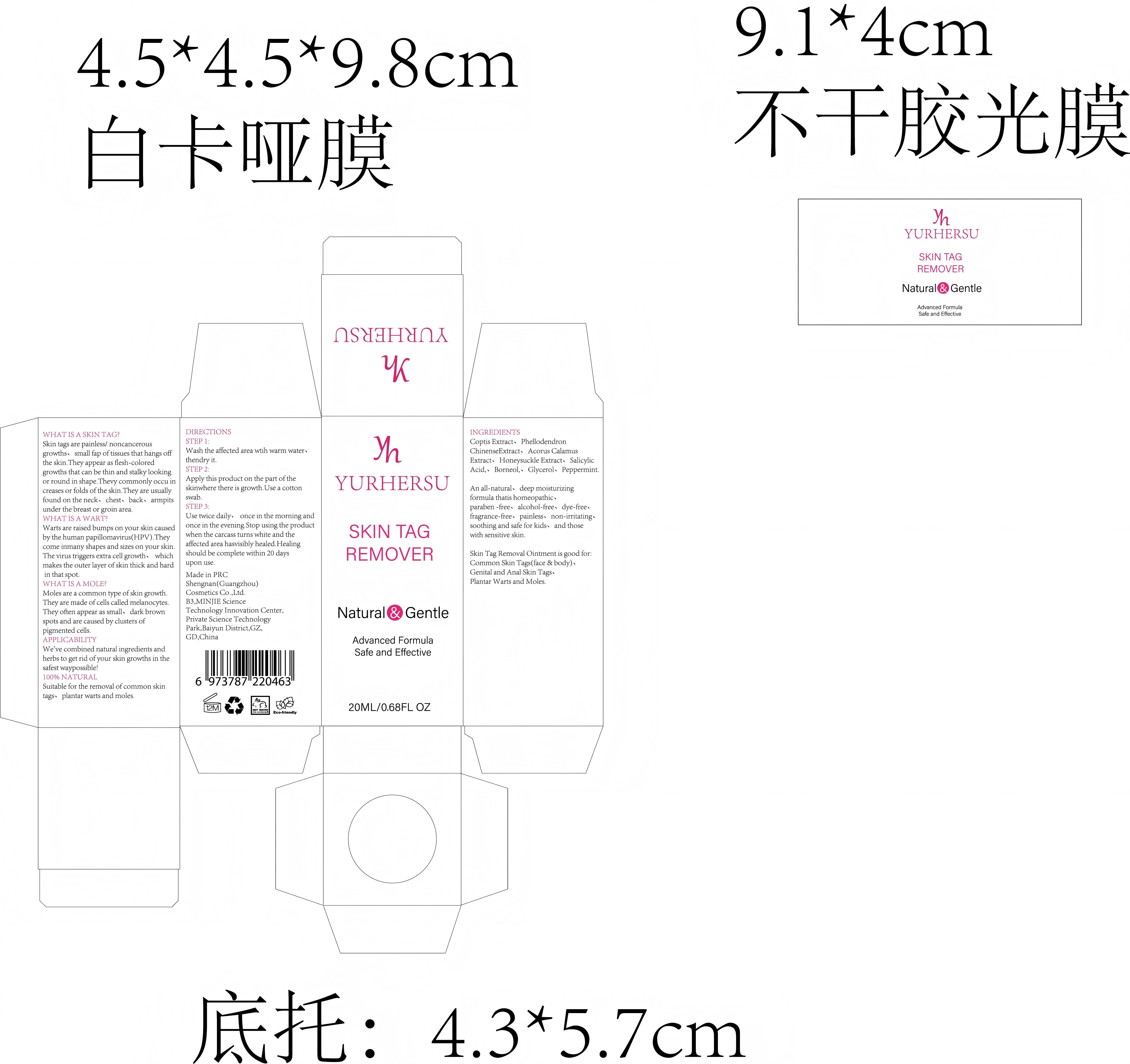 DRUG LABEL: SKIN TAG REMOVER
NDC: 84019-036 | Form: LIQUID
Manufacturer: Shengnan (Guangzhou) Cosmetics Co., LTD
Category: otc | Type: HUMAN OTC DRUG LABEL
Date: 20250916

ACTIVE INGREDIENTS: SALICYLIC ACID 100 mg/1 g
INACTIVE INGREDIENTS: GLYCERIN; BORNEOL

SKIN TAG REMOVER 20ml

WARNINGS

Please keep out of reach of children.

PURPOSE

Skin Tag Removal Ointment is good for:Common Skin Tags(face & body)、Genital and Anal Skin Tags、Plantar Warts and Moles.

STOP USE

This product is only applied to the surface of the skin and can not be taken orally, lf you feel unwell, please stop using immediately.

ACTIVE INGREDIENT

Salicylic Acid

WHEN USING

Please keep your skin dry before use to ensure the best results fromthe product.

INACTIVE INGREDIENT

Glycerin、Borneol、Mentha Piperita (Peppermint) Extract、Coptis Chinensis Root Extract、Phellodendron Amurense Leaf Extract、Acorus Calamus Root Extract、Lonicera Japonica (Honeysuckle) Leaf Extract

DOSAGE AND ADMINISTRATION

Apply 2 times a day

INDICATIONS AND USAGE

STEP 1:Wash the affected area wtih warm water、thendry it.STEP 2:Apply this product on the part oftheskinwhere there is growth.Use a cottonswab.STEP 3:Use twice daily、 once in the morning andonce in the evening.Stop using the product when the carcass turns white and the
affected area hasvisibly healed.Healingshould be complete within 20 days upon use.

OTC - KEEP OUT OF REACH OF CHILDREN SECTION